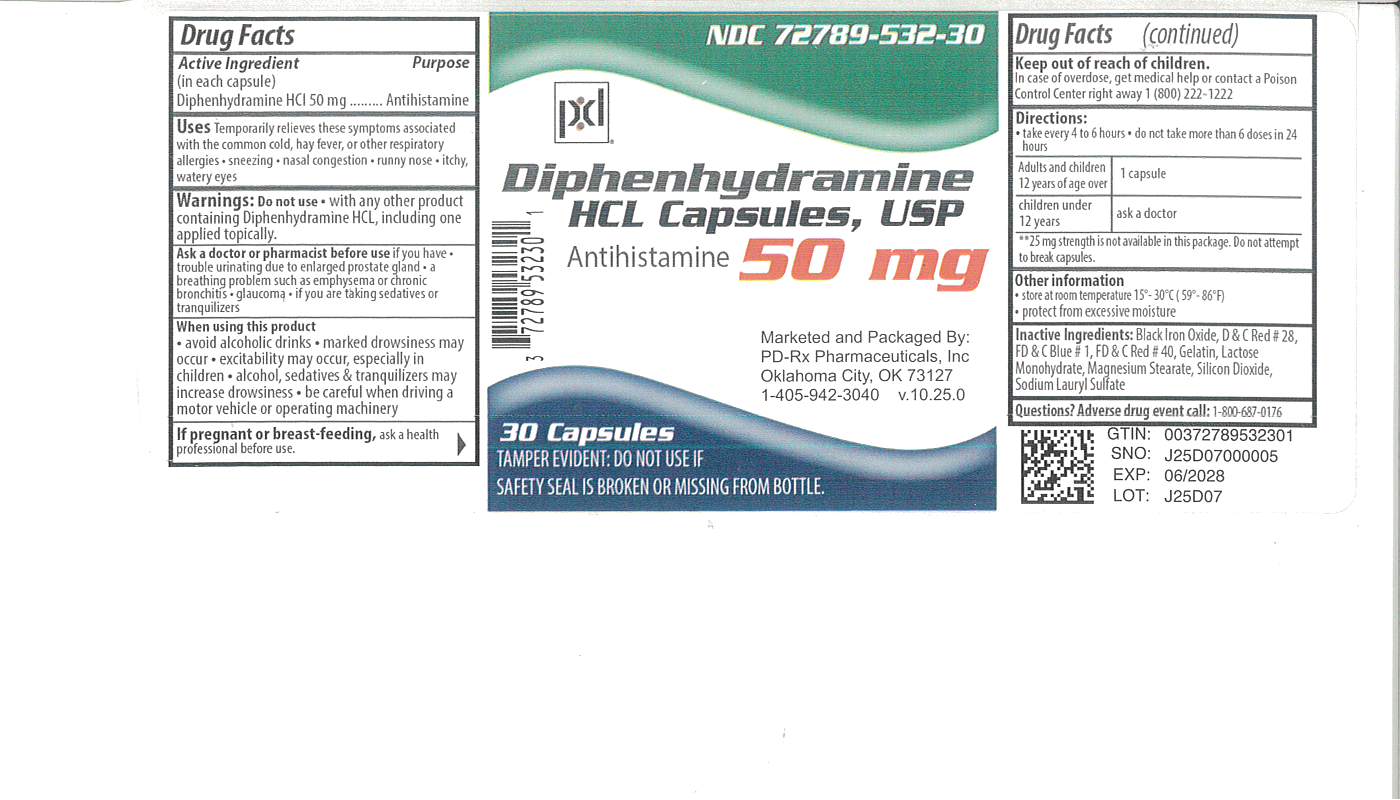 DRUG LABEL: Diphenhydramine HCL
NDC: 72789-532 | Form: CAPSULE
Manufacturer: PD-Rx Pharmaceuticals, Inc.
Category: otc | Type: HUMAN OTC DRUG LABEL
Date: 20251113

ACTIVE INGREDIENTS: DIPHENHYDRAMINE HYDROCHLORIDE 50 mg/1 1
INACTIVE INGREDIENTS: FERROSOFERRIC OXIDE; D&C RED NO. 28; FD&C BLUE NO. 1; FD&C RED NO. 40; GELATIN; LACTOSE MONOHYDRATE; MAGNESIUM STEARATE; SILICON DIOXIDE; SODIUM LAURYL SULFATE

Drug Facts

Active ingredient (in each capsule)

Diphenhydramine HCL 50 mg

Purpose

Antihistamine

Uses:

Temporarily relieves these symptoms associated with the common cold, hay fever, or other respiratory allergies

- sneezing
- nasal congestion
- runny nose
- itchy, watery eyes

Do not use

- With any other product containing Diphenhydramine HCL, including one applied topically.

Ask a doctor or pharmacist before use

If you have

- trouble urinating due to enlarged prostate gland
- a breathing problem such as emphysema or chronic bronchitis
- glaucoma
- if you are taking sedatives or tranquilizers

When using this product

- avoid alcoholic drinks
- marked drowsiness may occur
- excitability may occur, especially in children
- alcohol, sedatives and tranquilizers may increase drowsiness
- be careful when driving a motor vehicle or operating machinery

If pregnant or breast-feeding,

ask a health professional before use.

Keep out of reach of children

In case of overdose, get medical help or contact a Poison Control Center right away 1(800) 222-1222.

Directions:

- Take every 4-6 hours
- Do not take more than 6 doses in 24 hours.

Adults and children 12 years & over | 1 capsule
Children under 12 years | ask a doctor

**25 mg strength is not available in this package. Do not attempt to break capsules.

Other information:

- Store at room temperature 15-30 degrees C (59-86 degrees F)
- Protect from excessive moisture

Inactive ingredients:

Black Iron Oxide, D & C Red #28, FD & C Blue #1, FD & C Red #40, Gelatin, Lactose Monohydrate, Magnesium Stearate, Silicon Dioxide, Sodium Lauryl Sulfate

Questions? Adverse drug event call:

1-800-687-0176

PACKAGE LABEL

Diphenhydramine

HCl Capsules, USP

50 mg

TAMPER-EVIDENT: DO NOT USE IF SAFETY

SEAL IS BROKEN OR MISSING FROM BOTTLE

ANTIHISTAMINE